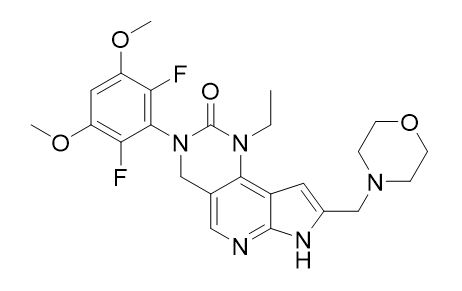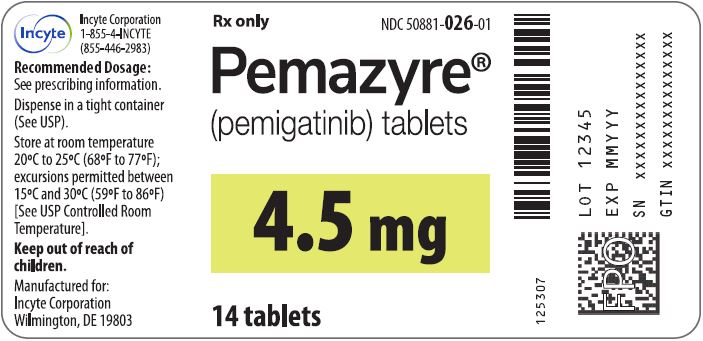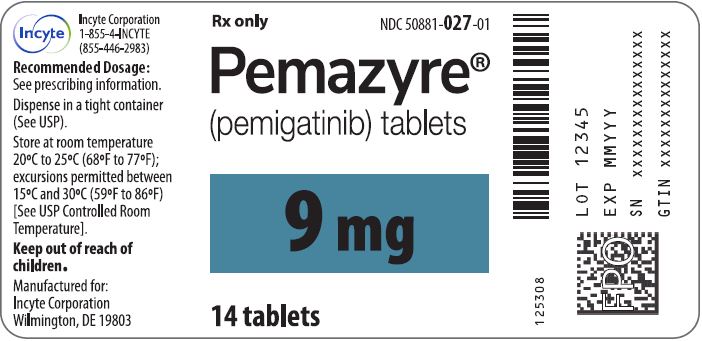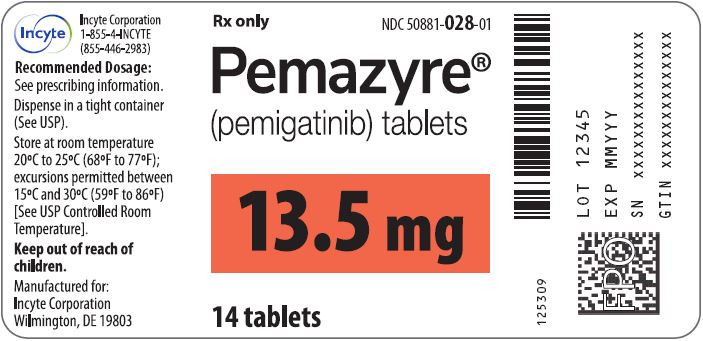 DRUG LABEL: PEMAZYRE
NDC: 50881-026 | Form: TABLET
Manufacturer: Incyte Corporation
Category: prescription | Type: HUMAN PRESCRIPTION DRUG LABEL
Date: 20250613

ACTIVE INGREDIENTS: PEMIGATINIB 4.5 mg/1 1
INACTIVE INGREDIENTS: CELLULOSE, MICROCRYSTALLINE; SODIUM STARCH GLYCOLATE TYPE A POTATO; MAGNESIUM STEARATE

HIGHLIGHTS OF PRESCRIBING INFORMATION

These highlights do not include all the information needed to use PEMAZYRE safely and effectively. See full prescribing information for PEMAZYRE.
PEMAZYRE® (pemigatinib) tablets, for oral use
Initial U.S. Approval: 2020

RECENT MAJOR CHANGES

Indications and Usage, Myeloid/Lymphoid Neoplasms with FGFR1 Rearrangement (1.2) | 8/2022
Dosage and Administration, Recommended Dosage (2.2) | 8/2022
Warnings and Precautions, Ocular Toxicity (5.1) | 8/2022
Warnings and Precautions, Hyperphosphatemia and Soft Tissue Mineralization (5.2) | 8/2022

1 INDICATIONS AND USAGE

PEMAZYRE is a kinase inhibitor indicated:

- for the treatment of adults with previously treated, unresectable locally advanced or metastatic cholangiocarcinoma with a fibroblast growth factor receptor 2 (FGFR2) fusion or other rearrangement as detected by an FDA-approved test. (1, 2.1)
  This indication is approved under accelerated approval based on overall response rate and duration of response. Continued approval for this indication may be contingent upon verification and description of clinical benefit in a confirmatory trial(s). (1, 2.1)
- For the treatment of adults with relapsed or refractory myeloid/lymphoid neoplasms (MLNs) with FGFR1 rearrangement. (1, 2.1)

2 DOSAGE AND ADMINISTRATION

Cholangiocarcinoma:

- Confirm the presence of an FGFR2 fusion or rearrangement prior to initiation of treatment with PEMAZYRE. (2.1)
- Recommended dosage is 13.5 mg orally once daily for 14 consecutive days followed by 7 days off therapy in 21-day cycles. Continue treatment until disease progression or unacceptable toxicity occurs. (2.2)

Myeloid/lymphoid neoplasms with FGFR1 rearrangement:

- Recommended dosage is 13.5 mg orally once daily. Continue treatment until disease progression or unacceptable toxicity. (2.2)

All patients treated with PEMAZYRE:

- Swallow tablet whole, with or without food. (2.2)
- Severe Renal Impairment: the recommended dosage of PEMAZYRE is 9 mg with the schedule (intermittent or continuous) designated for the indication. (2.5, 8.6, 12.3)
- Severe Hepatic Impairment: the recommended dosage of PEMAZYRE is 9 mg with the schedule (intermittent or continuous) designated for the indication. (2.6, 8.7, 12.3)

3 DOSAGE FORMS AND STRENGTHS

Tablets: 4.5 mg, 9 mg, and 13.5 mg. (3)

4 CONTRAINDICATIONS

None. (4)

5 WARNINGS AND PRECAUTIONS

- Ocular Toxicity: PEMAZYRE can cause retinal pigment epithelial detachment. Perform ophthalmological examination including optical coherence tomography (OCT) prior to initiation of therapy, every 2 months for the first 6 months of treatment and every 3 months thereafter, and urgently at any time for visual symptoms. (2.3, 5.1)
- Hyperphosphatemia and Soft Tissue Mineralization: PEMAZYRE can cause hyperphosphatemia leading to soft tissue mineralization, cutaneous calcification, calcinosis, and non-uremic calciphylaxis. Monitor for hyperphosphatemia and withhold, reduce the dose, or permanently discontinue based on duration and severity of hyperphosphatemia. (2.3, 5.2)
- Embryo-Fetal Toxicity: Can cause fetal harm. Advise patients of reproductive potential of the potential risk to the fetus and use effective contraception. (5.3, 8.1, 8.3)

6 ADVERSE REACTIONS

- Cholangiocarcinoma: The most common adverse reactions (incidence ≥ 20%) are hyperphosphatemia, alopecia, diarrhea, nail toxicity, fatigue, dysgeusia, nausea, constipation, stomatitis, dry eye, dry mouth, decreased appetite, vomiting, arthralgia, abdominal pain, hypophosphatemia, back pain, and dry skin. (6.1)
- Myeloid/lymphoid neoplasms with FGFR1 rearrangement: The most common (≥ 20%) adverse reactions are hyperphosphatemia, nail toxicity, alopecia, stomatitis, diarrhea, dry eye, fatigue, rash, abdominal pain, anemia, constipation, dry mouth, epistaxis, serous retinal detachment, extremity pain, decreased appetite, dry skin, dyspepsia, back pain, nausea, blurred vision, peripheral edema, and dizziness. (6.1)
  To report SUSPECTED ADVERSE REACTIONS, contact Incyte Corporation at 1-855-463-3463 or FDA at 1-800-FDA-1088 or www.fda.gov/medwatch.

7 DRUG INTERACTIONS

- Strong and Moderate CYP3A Inducers: Avoid concomitant use of PEMAZYRE. (7.1)
- Strong and Moderate CYP3A Inhibitors: Avoid concomitant use. If concomitant use cannot be avoided, reduce PEMAZYRE dosage. (2.4, 7.1)

8 USE IN SPECIFIC POPULATIONS

- Lactation: Advise not to breastfeed. (8.2)

FULL PRESCRIBING INFORMATION

1 INDICATIONS AND USAGE

1.1 Cholangiocarcinoma

PEMAZYRE is indicated for the treatment of adults with previously treated, unresectable locally advanced or metastatic cholangiocarcinoma with a fibroblast growth factor receptor 2 (FGFR2) fusion or other rearrangement as detected by an FDA-approved test [see Dosage and Administration (2.1)].

This indication is approved under accelerated approval based on overall response rate and duration of response [see Clinical Studies (14.1)]. Continued approval for this indication may be contingent upon verification and description of clinical benefit in a confirmatory trial(s).

1.2 Myeloid/Lymphoid Neoplasms with FGFR1 Rearrangement

PEMAZYRE is indicated for the treatment of adults with relapsed or refractory myeloid/lymphoid neoplasms (MLNs) with fibroblast growth factor receptor 1 (FGFR1) rearrangement.

2 DOSAGE AND ADMINISTRATION

2.1 Patient Selection

Select patients for the treatment of locally advanced or metastatic cholangiocarcinoma with PEMAZYRE based on the presence of an FGFR2 fusion or rearrangement as detected by an FDA-approved test [see Clinical Studies (14.1)].

Information on FDA-approved test(s) for the detection of an FGFR2 fusion or rearrangement in cholangiocarcinoma is available at http://www.fda.gov/CompanionDiagnostics.

Select patients for the treatment of relapsed or refractory myeloid/lymphoid neoplasms with FGFR1 rearrangement with PEMAZYRE based on the presence of an FGFR1 rearrangement [see Clinical Studies (14.2)]. An FDA-approved test for detection of FGFR1 rearrangement in patients with relapsed or refractory myeloid/lymphoid neoplasm for selecting patients for treatment with PEMAZYRE is not available.

2.2 Recommended Dosage

Take PEMAZYRE with or without food at approximately the same time every day [see Clinical Pharmacology (12.3)].

Swallow tablets whole. Do not crush, chew, split, or dissolve tablets.

If the patient misses a dose of PEMAZYRE by 4 or more hours or if vomiting occurs, resume dosing with the next scheduled dose.

Cholangiocarcinoma
The recommended dosage of PEMAZYRE is 13.5 mg orally once daily for 14 consecutive days followed by 7 days off therapy, in 21-day cycles. Continue treatment until disease progression or unacceptable toxicity occurs.

Myeloid/Lymphoid Neoplasms with FGFR1 Rearrangement
The recommended dosage of PEMAZYRE is 13.5 mg orally once daily on a continuous basis. Continue treatment until disease progression or unacceptable toxicity occurs.

2.3 Dosage Modification for Adverse Reactions

The recommended dose reductions for adverse reactions are provided in Table 1.

Table 1: Recommended Dose Reductions for PEMAZYRE for Adverse Reactions
Dose Reduction | Recommended Dosage
Dose Reduction | Cholangiocarcinoma with FGFR2 Fusion or Rearrangement | MLNs with FGFR1 Rearrangement
First | 9 mg once daily for first 14 days of each 21-day cycle | 9 mg once daily
Second | 4.5 mg once daily for first 14 days of each 21-day cycle | 4.5 mg once daily
Third | Discontinue | 4.5 mg once daily for first 14 days of each 21-day cycle [Permanently discontinue PEMAZYRE if unable to tolerate 4.5 mg once daily for 14 days of each 21-day cycle.]

The recommended dosage modifications for adverse reactions are provided in Table 2.

Table 2: Recommended Dosage Modifications for PEMAZYRE Adverse Reactions
Adverse Reaction | Severity [Severity as defined by National Cancer Institute Common Terminology Criteria for Adverse Events (NCI CTCAE) version 4.03.] | PEMAZYRE Dosage Modification
Retinal Pigment Epithelial Detachment (RPED) [see Warnings and Precautions (5.1)] | RPED | - If asymptomatic and stable on serial examination, continue PEMAZYRE. - If symptomatic or worsening on serial examination, withhold PEMAZYRE. - If asymptomatic and improved on subsequent examination, resume PEMAZYRE at a lower dose - If symptoms persist or examination does not improve, consider permanent discontinuation of PEMAZYRE, based on clinical status.
Hyperphosphatemia [see Warnings and Precautions (5.2)] | Serum phosphate > 7 mg/dL to ≤ 10 mg/dL | - Initiate phosphate lowering therapy and monitor serum phosphate weekly. - Withhold PEMAZYRE if levels are not < 7 mg/dL within 2 weeks of starting phosphate lowering therapy. - Resume PEMAZYRE at the same dose when phosphate levels are < 7 mg/dL for first occurrence; resume at a lower dose level for subsequent recurrences.
Hyperphosphatemia [see Warnings and Precautions (5.2)] | Serum phosphate >10 mg/dL | - Initiate phosphate lowering therapy and monitor serum phosphate weekly. - Withhold PEMAZYRE if levels are not ≤ 10 mg/dL within 1 week after starting phosphate lowering therapy. - Resume PEMAZYRE at the next lower dose level when phosphate levels are < 7 mg/dL. - Permanently discontinue PEMAZYRE for recurrence of serum phosphate > 10 mg/dL following 2 dose reductions.
Other Adverse Reactions | Grade 3 | - Withhold PEMAZYRE until resolves to Grade 1 or baseline. - Resume PEMAZYRE at next lower dose if resolves within 2 weeks. - Permanently discontinue PEMAZYRE if does not resolve within 2 weeks. - Permanently discontinue PEMAZYRE for recurrent Grade 3 after 2 dose reductions.
Other Adverse Reactions | Grade 4 | - Permanently discontinue PEMAZYRE.

2.4 Dosage Modification for Concomitant Use with Strong or Moderate CYP3A Inhibitors

Avoid concomitant use of strong and moderate CYP3A inhibitors with PEMAZYRE. If concomitant use with a strong or moderate CYP3A inhibitor cannot be avoided:

- Reduce PEMAZYRE dosage from 13.5 mg to 9 mg.
- Reduce PEMAZYRE dosage from 9 mg to 4.5 mg.

If concomitant use of a strong or moderate CYP3A inhibitor is discontinued, increase the PEMAZYRE dosage (after 3 plasma half-lives of the CYP3A inhibitor) to the dosage that was used before starting the strong or moderate inhibitor [see Clinical Pharmacology (12.3)].

2.5 Recommended Dosage for Severe Renal Impairment

The recommended dosage of PEMAZYRE for patients with severe renal impairment (eGFR estimated by Modification of Diet in Renal Disease [MDRD] 15 mL/min/1.73 m^2 to 29 mL/min/1.73 m^2) is 9 mg with the schedule (intermittent or continuous) designated for the indication [see Dosage and Administration (2.2), Use in Specific Populations (8.6) and Clinical Pharmacology (12.3)].

2.6 Recommended Dosage for Severe Hepatic Impairment

The recommended dosage of PEMAZYRE for patients with severe hepatic impairment (total bilirubin > 3 × ULN with any AST) is 9 mg with the schedule (intermittent or continuous) designated for the indication [see Dosage and Administration (2.2), Use in Specific Populations (8.7) and Clinical Pharmacology (12.3)].

3 DOSAGE FORMS AND STRENGTHS

Tablets:

- 4.5 mg: round, white to off-white tablet debossed on one side with "I" and "4.5" on the other side.
- 9 mg: oval, white to off-white tablet debossed on one side with "I" and "9" on the other side.
- 13.5 mg: round, white to off-white tablet debossed on one side with "I" and "13.5" on the other side.

4 CONTRAINDICATIONS

None.

5 WARNINGS AND PRECAUTIONS

5.1 Ocular Toxicity

Retinal Pigment Epithelial Detachment (RPED)

PEMAZYRE can cause RPED, which may cause symptoms such as blurred vision, visual floaters, or photopsia. Clinical trials of PEMAZYRE did not conduct routine monitoring including optical coherence tomography (OCT) to detect asymptomatic RPED; therefore, the incidence of asymptomatic RPED with PEMAZYRE is unknown.

Among 635 patients who received a starting dose of PEMAZYRE 13.5 mg across clinical trials, RPED occurred in 11% of patients, including Grade 3-4 RPED in 1.3%. The median time to first onset of RPED was 56 days. RPED led to dose interruption of PEMAZYRE in 3.1% of patients, and dose reduction and permanent discontinuation in 1.3% and in 0.2% of patients, respectively. RPED resolved or improved to Grade 1 levels in 76% of patients who required dosage modification of PEMAZYRE for RPED.

Perform a comprehensive ophthalmological examination including OCT prior to initiation of PEMAZYRE and every 2 months for the first 6 months and every 3 months thereafter during treatment. For onset of visual symptoms, refer patients for ophthalmologic evaluation urgently, with follow-up every 3 weeks until resolution or discontinuation of PEMAZYRE.

Modify the dose or permanently discontinue PEMAZYRE as recommended [see Dosage and Administration (2.3)].

Dry Eye

Among 635 patients who received a starting dose of PEMAZYRE 13.5 mg across clinical trials, dry eye occurred in 31% of patients, including Grade 3-4 in 1.6% of patients. Treat patients with ocular demulcents as needed.

5.2 Hyperphosphatemia and Soft Tissue Mineralization

PEMAZYRE can cause hyperphosphatemia leading to soft tissue mineralization, cutaneous calcification, calcinosis, and non-uremic calciphylaxis. Increases in phosphate levels are a pharmacodynamic effect of PEMAZYRE [see Clinical Pharmacology (12.2)]. Among 635 patients who received a starting dose of PEMAZYRE 13.5 mg across clinical trials, hyperphosphatemia was reported in 93% of patients based on laboratory values above the upper limit of normal. The median time to onset of hyperphosphatemia was 8 days (range 1-169). Phosphate lowering therapy was required in 33% of patients receiving PEMAZYRE.

Monitor for hyperphosphatemia and initiate a low phosphate diet when serum phosphate level is > 5.5 mg/dL. For serum phosphate levels > 7 mg/dL, initiate phosphate lowering therapy and withhold, reduce the dose, or permanently discontinue PEMAZYRE based on duration and severity of hyperphosphatemia [see Dosage and Administration (2.3)].

5.3 Embryo-Fetal Toxicity

Based on findings in an animal study and its mechanism of action, PEMAZYRE can cause fetal harm when administered to a pregnant woman. Oral administration of pemigatinib to pregnant rats during the period of organogenesis caused fetal malformations, fetal growth retardation, and embryo-fetal death at maternal exposures lower than the human exposure based on area under the curve (AUC) at the clinical dose of 13.5 mg.

Advise pregnant women of the potential risk to the fetus. Advise female patients of reproductive potential to use effective contraception during treatment with PEMAZYRE and for 1 week after the last dose. Advise males with female partners of reproductive potential to use effective contraception during treatment with PEMAZYRE and for 1 week after the last dose [see Use in Specific Populations (8.1, 8.3)].

6 ADVERSE REACTIONS

The following adverse reactions are discussed elsewhere in the labeling:

- Ocular Toxicity [see Warnings and Precautions (5.1)]
- Hyperphosphatemia and Soft Tissue Mineralization [see Warnings and Precautions (5.2)]

6.1 Clinical Trials Experience

Because clinical trials are conducted under widely varying conditions, adverse reaction rates observed in the clinical trials of a drug cannot be directly compared to rates in the clinical trials of another drug and may not reflect the rates observed in practice.

The pooled safety population described in the WARNINGS AND PRECAUTIONS section reflects exposure to PEMAZYRE at a starting dose of 13.5 mg orally once daily (intermittent or continuous administration) in 635 patients with advanced malignancies. Among the 635 patients, 31% were exposed for 6 months or longer and 11% were exposed greater than one year, including patients with previously treated, advanced, or metastatic cholangiocarcinoma in FIGHT-202 and patients with MLNs with FGFR1 rearrangement in FIGHT-203.

Cholangiocarcinoma

FIGHT-202

The safety of PEMAZYRE was evaluated in FIGHT-202, which included 146 patients with previously treated, locally advanced or metastatic cholangiocarcinoma [see Clinical Studies (14.1)]. Patients were treated orally with PEMAZYRE 13.5 mg once daily for 14 days on followed by 7 days off therapy until disease progression or unacceptable toxicity. The median duration of treatment was 181 days (range: 7 to 730 days).

The median age of PEMAZYRE-treated patients was 59 years (range 26-78), 58% were females, and 71% were White.

Serious adverse reactions occurred in 45% of patients receiving PEMAZYRE. Serious adverse reactions in ≥ 2% of patients who received PEMAZYRE included abdominal pain, pyrexia, cholangitis, pleural effusion, acute kidney injury, cholangitis infective, failure to thrive, hypercalcemia, hyponatremia, small intestinal obstruction, and urinary tract infection. Fatal adverse reactions occurred in 4.1% of patients, including failure to thrive, bile duct obstruction, cholangitis, sepsis, and pleural effusion.

Permanent discontinuation due to an adverse reaction occurred in 9% of patients who received PEMAZYRE. Adverse reactions requiring permanent discontinuation in ≥ 1% of patients included intestinal obstruction and acute kidney injury.

Dosage interruptions due to an adverse reaction occurred in 43% of patients who received PEMAZYRE. Adverse reactions requiring dosage interruption in ≥ 1% of patients included stomatitis, palmar-plantar erythrodysesthesia syndrome, arthralgia, fatigue, abdominal pain, AST increased, asthenia, pyrexia, ALT increased, cholangitis, small intestinal obstruction, alkaline phosphatase increased, diarrhea, hyperbilirubinemia, electrocardiogram QT prolonged, decreased appetite, dehydration, hypercalcemia, hyperphosphatemia, hypophosphatemia, back pain, pain in extremity, syncope, acute kidney injury, onychomadesis, and hypotension.

Dose reductions due to an adverse reaction occurred in 14% of patients who received PEMAZYRE. Adverse reactions requiring dosage reductions in ≥ 1% of patients who received PEMAZYRE included stomatitis, arthralgia, palmar-plantar erythrodysesthesia syndrome, asthenia, and onychomadesis.

Table 3 summarizes the adverse reactions in FIGHT-202. Table 4 summarizes laboratory abnormalities in FIGHT-202.

Table 3: Adverse Reactions (≥ 15%) in Patients Receiving PEMAZYRE in FIGHT-202
Adverse Reaction | PEMAZYRE N=146
Adverse Reaction | All Grades [Graded per NCI CTCAE 4.03.] (%) | Grades 3 or 4 (%)
Metabolism and nutrition disorders
Hyperphosphatemia [Includes hyperphosphatemia and blood phosphorous increased; graded based on clinical severity and medical interventions taken according to the "investigations-other, specify" category in NCI CTCAE v4.03.] | 60 | 0
Decreased appetite | 33 | 1.4
Hypophosphatemia [Includes hypophosphatemia and blood phosphorous decreased.] | 23 | 12
Dehydration | 15 | 3.4
Skin and subcutaneous tissue disorders
Alopecia | 49 | 0
Nail toxicity [Includes nail toxicity, nail disorder, nail discoloration, nail dystrophy, nail hypertrophy, nail ridging, nail infection, onychalgia, onychoclasis, onycholysis, onychomadesis, onychomycosis, and paronychia.] | 43 | 2.1
Dry skin | 20 | 0.7
Palmar-plantar erythrodysesthesia syndrome | 15 | 4.1
Gastrointestinal disorders
Diarrhea | 47 | 2.7
Nausea | 40 | 2.1
Constipation | 35 | 0.7
Stomatitis | 35 | 5
Dry mouth | 34 | 0
Vomiting | 27 | 1.4
Abdominal pain | 23 | 4.8
General disorders
Fatigue | 42 | 4.8
Edema peripheral | 18 | 0.7
Nervous system disorders
Dysgeusia | 40 | 0
Headache | 16 | 0
Eye disorders
Dry eye [Includes dry eye, keratitis, lacrimation increased, pinguecula, and punctate keratitis.] | 35 | 0.7
Musculoskeletal and connective tissue disorders
Arthralgia | 25 | 6
Back pain | 20 | 2.7
Pain in extremity | 19 | 2.1
Infections and infestations
Urinary tract infection | 16 | 2.7
Investigations
Weight loss | 16 | 2.1

Clinically relevant adverse reactions occurring in ≤ 10% of patients included fractures (2.1%). In all patients treated with pemigatinib, 0.5% experienced pathologic fractures (which included patients with and without cholangiocarcinoma [N=635]). Soft tissue mineralization, including cutaneous calcification, calcinosis, and non-uremic calciphylaxis associated with hyperphosphatemia were observed with PEMAZYRE treatment.

Table 4: Select Laboratory Abnormalities (≥ 10%) Worsening from Baseline in Patients Receiving PEMAZYRE in FIGHT-202
 | PEMAZYRE [The denominator used to calculate the rate varied from 142-146 based on the number of patients with a baseline value and at least one post-treatment value.] N=146
Laboratory Abnormality | All Grades [Graded per NCI CTCAE 4.03.] (%) | Grades 3 or 4 (%)
Hematology
Decreased hemoglobin | 43 | 6
Decreased lymphocytes | 36 | 8
Decreased platelets | 28 | 3.4
Increased leukocytes | 27 | 0.7
Decreased leukocytes | 18 | 1.4
Chemistry
Increased phosphate [Based on CTCAE 5.0 grading.] | 94 | 0
Decreased phosphate | 68 | 38
Increased alanine aminotransferase | 43 | 4.1
Increased aspartate aminotransferase | 43 | 6
Increased calcium | 43 | 4.1
Increased alkaline phosphatase | 41 | 11
Increased creatinine [Graded based on comparison to upper limit of normal.] | 41 | 1.4
Decreased sodium | 39 | 12
Increased glucose | 36 | 0.7
Decreased albumin | 34 | 0
Increased urate | 30 | 10
Increased bilirubin | 26 | 6
Decreased potassium | 26 | 5
Decreased calcium | 17 | 2.7
Increased potassium | 12 | 2.1
Decreased glucose | 11 | 1.4

Increased Creatinine

Within the first 21-day cycle of PEMAZYRE dosing, serum creatinine increased (mean increase of 0.2 mg/dL) and reached steady state by Day 8, and then decreased during the 7 days off therapy. Consider alternative markers of renal function if persistent elevations in serum creatinine are observed [see Clinical Pharmacology (12.3)].

Myeloid/Lymphoid Neoplasms with FGFR1 Rearrangement

FIGHT-203

The safety of PEMAZYRE was evaluated in FIGHT-203, which included 34 patients who were treated for MLN with FGFR1 rearrangement [see Clinical Studies (14.2)]. Patients were treated with PEMAZYRE 13.5 mg once daily on a continuous schedule (the approved recommended starting dosage) or for 14 days on followed by 7 days off therapy (an unapproved dosage regimen in MLN with FGFR1 rearrangement) until disease progression, unacceptable toxicity, or they were able to receive allogeneic stem cell transplant. The median duration of treatment was 205 days (range: 30-1347 days).

Serious adverse reactions occurred in 53% of patients receiving PEMAZYRE at all dosages. Serious adverse reactions in > 5% of patients included acute kidney injury. Fatal adverse reactions occurred in 9% of patients who received PEMAZYRE, including acute kidney injury, multiple organ dysfunction syndrome, and malignant neoplasm progression, occurring in one patient each.

Permanent discontinuation due to an adverse reaction occurred in 12% of patients who received PEMAZYRE at all dosages. Adverse reactions requiring permanent discontinuation included cardiac failure, multiple organ dysfunction syndrome, blood alkaline phosphatase increase, and calciphylaxis.

In patients who started treatment on the recommended dosage (n = 20), adverse reactions requiring dosage interruption of PEMAZYRE occurred in 80% of patients. Adverse reactions which required dosage interruption in > 2 patients treated at the recommended dosage included nail toxicities (20%) and hyperphosphatemia (15%).

Dose reductions of PEMAZYRE due to an adverse reaction occurred in 80% of patients who started treatment on the recommended dosage. Adverse reactions requiring dose reductions occurring in > 2 patients were nail toxicities (20%), hyperphosphatemia (20%), and alopecia (15%).

The most common (≥ 20%) adverse reactions were hyperphosphatemia, nail toxicity, alopecia, stomatitis, diarrhea, dry eye, fatigue, rash, abdominal pain, anemia, constipation, dry mouth, epistaxis, serous retinal detachment, extremity pain, decreased appetite, dry skin, dyspepsia, back pain, nausea, blurred vision, peripheral edema, and dizziness.

The most common (≥ 20%) laboratory abnormalities were increased phosphate, decreased lymphocytes, decreased leukocytes, increased alkaline phosphatase, decreased hemoglobin, increased alanine aminotransferase, increased aspartate aminotransferase, decreased neutrophils, increased creatinine, decreased phosphate, decreased sodium, increased glucose, decreased platelets, decreased calcium, increased calcium, decreased potassium, and increased bilirubin.

Table 5 summarizes the adverse reactions in FIGHT-203.

Table 5: Adverse Reactions (≥ 15%) in Patients Receiving PEMAZYRE in FIGHT-203
Adverse Reaction | PEMAZYRE N=34
Adverse Reaction | All Grades [Graded per NCI CTCAE 4.03.] (%) | Grade 3 or 4 (%)
Metabolism and nutrition disorders
Hyperphosphatemia [Includes hyperphosphatemia and blood phosphorous increased; graded based on clinical severity and medical interventions taken according to the "investigations-other, specify" category in NCI CTCAE v4.03.] | 74 | 2.9
Decreased appetite | 24 | 6
Skin and subcutaneous tissue disorders
Nail toxicity [Includes ingrowing nail, nail bed inflammation, nail bed tenderness, nail discoloration, nail disorder, nail dystrophy, nail growth abnormal, nail infection, nail pigmentation, onychalgia, onychoclasis, onycholysis, onychomadesis, onychomycosis, and paronychia.] | 62 | 21
Alopecia | 59 | 0
Rash [Includes dermatitis, dermatitis acneiform, lichen planus, rash, rash macular, and skin exfoliation.] | 35 | 6
Dry skin [Includes dry skin and xerosis.] | 24 | 0
Palmar-plantar erythrodysaesthesia [Includes palmar erythema, palmar-plantar erythrodysaesthesia, and plantar erythema.] | 18 | 9
Gastrointestinal disorders
Stomatitis [Includes aphthous ulcer, cheilitis, lip ulceration, mouth ulceration, pharyngeal inflammation, stomatitis, and tongue ulceration.] | 53 | 15
Diarrhea | 50 | 2.9
Abdominal pain [Includes abdominal pain, abdominal pain lower, abdominal pain upper, and abdominal rigidity.] | 35 | 2.9
Constipation | 32 | 2.9
Dry mouth | 32 | 0
Dyspepsia | 24 | 0
Nausea | 21 | 0
Eye disorders
Dry eye [Includes dry eye, keratitis, lacrimation increased, meibomian gland dysfunction, and punctate keratitis] | 50 | 6
Retinal pigment epithelial detachment [Includes detachment of retinal pigment epithelium, maculopathy, retinal detachment, retinal disorder, retinal thickening, serous retinal detachment, and subretinal fluid.] | 26 | 0
Vision blurred | 21 | 2.9
Trichiasis | 18 | 2.9
General disorders
Fatigue [Includes asthenia and fatigue.] | 44 | 9
Edema peripheral | 21 | 0
Pyrexia | 18 | 2.9
Blood and lymphatic system disorders
Anemia | 35 | 18
Respiratory, thoracic, and mediastinal disorders
Epistaxis | 29 | 0
Musculoskeletal and connective tissue disorders
Pain in extremity | 26 | 12
Back pain [Includes back pain and spinal pain.] | 24 | 9
Nervous system disorders
Dizziness | 21 | 0

Table 6 summarizes laboratory abnormalities in FIGHT-203.

Table 6: Select Laboratory Abnormalities (≥ 20%) Worsening from Baseline in Patients Receiving PEMAZYRE in FIGHT-203
Laboratory Abnormality | PEMAZYRE N=34 [The denominator used to calculate the rate varied from 31 to 34 based on the number of patients with a baseline value and at least one post-treatment value.]
Laboratory Abnormality | All Grades [Graded per NCI CTCAE 4.03.] (%) | Grade 3 or 4 (%)
Hematology
Decreased lymphocytes | 65 | 16
Decreased leukocytes | 65 | 15
Decreased hemoglobin | 53 | 9
Decreased neutrophils | 45 | 12
Decreased platelets | 29 | 15
Chemistry
Increased phosphate [Graded per NCI CTCAE 5.0.] | 97 | 2.9
Increased alkaline phosphatase | 62 | 9
Increased alanine aminotransferase | 50 | 12
Increased aspartate aminotransferase | 47 | 9
Increased creatinine [Based on comparison to upper limit of normal.] | 44 | 0
Decreased phosphate | 41 | 26
Decreased sodium | 41 | 9
Increased glucose | 33 | 3
Decreased calcium | 26 | 2.9
Increased calcium | 26 | 2.9
Decreased potassium | 24 | 2.9
Increased bilirubin | 21 | 0

Other clinically significant laboratory abnormalities: Prothrombin time/international normalized ratio was elevated in 16% (Grade 1 or 2 elevation) of patients. Uric acid was elevated in 18% of patients, including 2.9% with a Grade 3 or 4 elevation.

7 DRUG INTERACTIONS

7.1 Effect of Other Drugs on PEMAZYRE

Strong and Moderate CYP3A Inducers

Concomitant use of PEMAZYRE with a strong or moderate CYP3A inducer decreases pemigatinib plasma concentrations [see Clinical Pharmacology (12.3)], which may reduce the efficacy of PEMAZYRE. Avoid concomitant use of strong and moderate CYP3A inducers with PEMAZYRE.

Strong and Moderate CYP3A Inhibitors

Concomitant use of a strong or moderate CYP3A inhibitor with PEMAZYRE increases pemigatinib plasma concentrations [see Clinical Pharmacology (12.3)], which may increase the incidence and severity of adverse reactions. Avoid concomitant use of strong and moderate CYP3A inhibitors with PEMAZYRE. Reduce PEMAZYRE dosage if concomitant use of strong and moderate CYP3A inhibitors cannot be avoided [see Dosage and Administration (2.4)].

8 USE IN SPECIFIC POPULATIONS

8.1 Pregnancy

Risk Summary

Based on findings in an animal study and its mechanism of action, PEMAZYRE can cause fetal harm or loss of pregnancy when administered to a pregnant woman [see Clinical Pharmacology (12.1)]. There are no available data on the use of PEMAZYRE in pregnant women. Oral administration of pemigatinib to pregnant rats during the period of organogenesis at maternal plasma exposures below the human exposure at the clinical dose of 13.5 mg resulted in fetal malformations, fetal growth retardation, and embryo-fetal death (see Data). Advise pregnant women of the potential risk to a fetus.

In the U.S. general population, the estimated background risk of major birth defects and miscarriage in clinically recognized pregnancies is 2% to 4% and 15% to 20%, respectively.

Data

Animal Data

Once daily oral administration of pemigatinib to pregnant rats during the period of organogenesis resulted in 100% embryofetal mortality due to post-implantation loss at doses ≥ 0.3 mg/kg (approximately 0.6 times the human exposure based on AUC at the clinical dose of 13.5 mg). Fetal survival was unaffected at 0.1 mg/kg per day; however, once daily oral administration of pemigatinib at the 0.1 mg/kg dose level (approximately 0.2 times the human exposure based on AUC at the clinical dose of 13.5 mg) resulted in reduced mean fetal body weight and an increase in fetal skeletal and visceral malformations, major blood vessel variations, and reduced ossification.

8.2 Lactation

Risk Summary

There are no data on the presence of pemigatinib or its metabolites in human milk or their effects on either the breastfed child or on milk production. Because of the potential for serious adverse reactions in breastfed children from PEMAZYRE, advise women not to breastfeed during treatment and for 1 week after the last dose.

8.3 Females and Males of Reproductive Potential

PEMAZYRE can cause fetal harm when administered to pregnant women [see Use in Specific Populations (8.1)].

Pregnancy Testing

Verify pregnancy status of females of reproductive potential prior to initiating PEMAZYRE [see Use in Specific Populations (8.1)].

Contraception

Females

Advise females of reproductive potential to use effective contraception during treatment with PEMAZYRE and for 1 week after the last dose.

Males

Advise males with female partners of reproductive potential to use effective contraception during treatment with PEMAZYRE and for 1 week after the last dose.

8.4 Pediatric Use

The safety and effectiveness of PEMAZYRE have not been established in pediatric patients.

Animal Toxicity Data

In 4- or 13-week repeat-dose toxicology studies in rats and non-human primates, animals displayed toxicities in bone and teeth at pemigatinib exposures lower than the human exposure at the clinical dose of 13.5 mg. Physeal and cartilage dysplasia were present in multiple bones in both species, and tooth (incisor) abnormalities (complete loss of ameloblasts with associated secondary changes) occurred in rats. Six weeks after cessation of dosing, these findings did not show complete evidence of recovery, and additional tooth-related findings (mal-aligned, whitened, broken, and trimmed/thinned incisors) developed in the 13-week study.

8.5 Geriatric Use

In FIGHT-202 in patients with cholangiocarcinoma, 32% of patients were 65 years and older, and 8% of patients were 75 years and older. In FIGHT-203 in patients with MLN with FGFR1 rearrangement, 44% of patients were 65 years and older, and 2.9% of patients were 75 years and older.

No overall differences in safety or effectiveness were observed between these patients and younger patients.

8.6 Renal Impairment

Reduce the recommended dosage of PEMAZYRE for patients with severe renal impairment (eGFR 15 to 29 mL/min/1.73 m^2, estimated by MDRD equation) [see Dosage and Administration (2.5) and Clinical Pharmacology (12.3)].

No dosage adjustment is recommended for patients with mild or moderate renal impairment (eGFR 30 to 89 mL/min/1.73 m^2). No dosage adjustment is recommended for patients with end-stage renal disease (eGFR < 15 mL/min/1.73 m^2) who are receiving intermittent hemodialysis [see Clinical Pharmacology (12.3)].

8.7 Hepatic Impairment

Reduce the recommended dosage of PEMAZYRE for patients with severe hepatic impairment (total bilirubin > 3 × ULN with any AST) [see Dosage and Administration (2.6) and Clinical Pharmacology (12.3)].

No dosage adjustment is recommended for patients with mild (total bilirubin > upper limit of normal [ULN] to 1.5 × ULN or AST > ULN) or moderate (total bilirubin >1.5–3 × ULN with any AST) hepatic impairment [see Clinical Pharmacology (12.3)].

11 DESCRIPTION

Pemigatinib is a kinase inhibitor with the chemical name 3-(2,6-difluoro-3,5-dimethoxyphenyl)-1-ethyl-8-(morpholin-4-ylmethyl)-1,3,4,7-tetrahydro-2H-pyrrolo[3',2':5,6]pyrido[4,3-d]pyrimidin-2-one. Pemigatinib has a molecular formula of C24H27F2N5O4 and molecular mass of 487.5 g/mole. Pemigatinib has the following chemical structure:

Pemigatinib is a white to off-white solid that is not hygroscopic. The solubility of pemigatinib is pH dependent with decreasing solubility observed with increasing pH. PEMAZYRE tablets are uncoated and for oral administration. Tablets are available containing 4.5 mg, 9 mg, or 13.5 mg of pemigatinib active ingredient. The inactive ingredients include magnesium stearate, microcrystalline cellulose, and sodium starch glycolate.

12 CLINICAL PHARMACOLOGY

12.1 Mechanism of Action

Pemigatinib is a small molecule kinase inhibitor that targets FGFR1, 2 and 3 with IC50 values of less than 2 nM. Pemigatinib also inhibited FGFR4 in vitro at a concentration approximately 100 times higher than those that inhibit FGFR1, 2, and 3. Pemigatinib inhibited FGFR1-3 phosphorylation and signaling and decreased cell viability in cancer cell lines with activating FGFR amplifications and fusions that resulted in constitutive activation of FGFR signaling. Constitutive FGFR signaling can support the proliferation and survival of malignant cells. Pemigatinib exhibited anti-tumor activity in mouse xenograft models of human tumors with FGFR1, FGFR2, or FGFR3 alterations resulting in constitutive FGFR activation including a patient-derived xenograft model of cholangiocarcinoma that expressed an oncogenic FGFR2-Transformer-2 beta homolog (TRA2b) fusion protein and the KG1 leukemia model that carries a translocation of FGFR1 (FGFR1OP2-FGFR1).

12.2 Pharmacodynamics

Serum Phosphate

Pemigatinib increased serum phosphate levels as a consequence of FGFR inhibition. Serum phosphate increased with increasing exposure across the dose range of 1 to 20 mg once daily (0.07 to 1.5 times the recommended dose), with increased risk of hyperphosphatemia with higher pemigatinib exposure.

Cardiac Electrophysiology

At a dose 1.5 times the maximum recommended dose, PEMAZYRE does not result in a large mean increase (i.e. > 20 ms) of the QTc interval.

12.3 Pharmacokinetics

The geometric mean (CV%) steady-state pemigatinib AUC0-24h was 2620 nM·h (54%) and Cmax was 236 nM (56%) for 13.5 mg orally once daily. Steady state pemigatinib concentrations increased proportionally over the dose range of 1 to 20 mg (0.07 to 1.5 times the recommended dose). Steady-state was achieved within 4 days and pemigatinib accumulated with a median accumulation ratio of 1.63 (range 0.63 to 3.28) following repeated once daily dosing.

Absorption

The median time to achieve peak pemigatinib plasma concentration (Tmax) was 1.13 (0.50‑6.00) hours.

Effect of Food

Administration of PEMAZYRE with a high-fat and high-calorie meal (approximately 1000 calories with 150 calories from protein, 250 calories from carbohydrate, and 500‑600 calories from fat) had no clinically significant effect on pemigatinib pharmacokinetics.

Distribution

The estimated apparent volume of distribution was 235 L (60.8%) following a 13.5 mg oral dose. Protein binding of pemigatinib was 90.6% and was independent of concentration in vitro.

Elimination

The geometric mean (%CV) elimination half-life (t½) of pemigatinib was 15.4 (51.6%) hours and the geometric mean apparent clearance (CL/F) was 10.6 L/h (54%).

Metabolism

Pemigatinib is predominantly metabolized by CYP3A4 in vitro. The major drug-related moiety in plasma was unchanged pemigatinib.

Excretion

Following a single oral 11 mg dose of radiolabeled pemigatinib, 82.4% of the dose was recovered in feces (1.4% as unchanged) and 12.6% in urine (1% as unchanged).

Specific Populations

No clinically significant differences in the systemic exposure of pemigatinib were observed based on age (21 ‑ 79 years), sex, race/ethnicity (White 68.2%, Asian 16%, Black 6.3%, Hispanic 6%, other 3.5%) or body weight (39.8 ‑ 156 kg).

Patients with Renal Impairment

No clinically significant differences in the systemic exposure of pemigatinib were observed in mild to moderate renal impairment (eGFR 30 to 89 mL/min, MDRD) or end-stage renal disease (eGFR <15 mL/min/1.73 m^2) on intermittent hemodialysis. Compared to subjects with normal renal function, the geometric mean pemigatinib AUC0–inf increased by 59% in patients with severe renal impairment (eGFR 15 to 29 mL/min/1.73 m^2).

Patients with Hepatic Impairment

No clinically significant differences in the systemic exposure of pemigatinib were observed in mild (total bilirubin > upper limit of normal [ULN] to 1.5 × ULN or AST > ULN) to moderate (total bilirubin >1.5–3 × ULN with any AST) hepatic impairment. Compared to subjects with normal hepatic function, the geometric mean pemigatinib AUC0–inf increased by 136% in subjects with severe hepatic impairment (total bilirubin > 3 × ULN with any AST).

Drug Interaction Studies

Clinical Studies and Model-Based Approaches

CYP3A Inhibitors: Itraconazole (strong CYP3A inhibitor) increased Cmax by 17% and increased AUC by 88% following a single oral PEMAZYRE dose of 4.5 mg [see Drug Interactions (7.1)]. Concomitant use of moderate CYP3A inhibitors is predicted to increase pemigatinib exposure by approximately 50-80% [see Drug Interactions (7.1)].

CYP3A Inducers: Rifampin (strong CYP3A inducer) decreased pemigatinib Cmax by 62% and AUC by 85% following a single oral PEMAZYRE dose of 13.5 mg [see Drug Interactions (7.1)]. Concomitant use of a moderate CYP3A inducer is predicted to decrease pemigatinib exposure by more than 50% [see Drug Interactions (7.1)].

Other Drugs: No clinically significant differences in pemigatinib exposure when co-administered with esomeprazole (proton pump inhibitor) or ranitidine (histamine-2 antagonist). No clinically significant differences in glucose levels were observed when metformin (OCT2/MATE1 substrate) was co-administered with pemigatinib.

In Vitro Studies

CYP Enzymes: Pemigatinib is not an inhibitor of CYP1A2, CYP2B6, CYP2C8, CYP2C9, CYP2C19, CYP2D6, or CYP3A4 or an inducer of CYP1A2, CYP2B6, or CYP3A4.

Transporter Systems: Pemigatinib is a substrate of both P-gp and BCRP. P-gp or BCRP inhibitors are not expected to affect pemigatinib exposure at clinically relevant concentrations. Pemigatinib is an inhibitor of P-gp, OCT2, and MATE1. Pemigatinib may increase serum creatinine by decreasing renal tubular secretion of creatinine; this may occur due to inhibition of renal transporters OCT2 and MATE1 and may not affect glomerular function [see Adverse Reactions (6.1)].

13 NONCLINICAL TOXICOLOGY

13.1 Carcinogenesis, Mutagenesis, Impairment of Fertility

Carcinogenicity studies have not been conducted with pemigatinib.

Pemigatinib was not mutagenic in an in vitro bacterial reverse mutation (Ames) assay and was not clastogenic in either an in vitro chromosome aberration assay or an in vivo micronucleus assay in rats.

Dedicated fertility studies with pemigatinib have not been conducted. Oral administration of pemigatinib did not result in any dose-related findings likely to result in impaired fertility in male and female reproductive organs.

14 CLINICAL STUDIES

14.1 Cholangiocarcinoma

FIGHT-202 (NCT02924376), a multicenter open-label single-arm trial, evaluated the efficacy of PEMAZYRE in 107 patients with locally advanced unresectable or metastatic cholangiocarcinoma whose disease had progressed on or after at least 1 prior therapy and who had an FGFR2 gene fusion or non-fusion rearrangement, as determined by a clinical trial assay performed at a central laboratory. Qualifying in-frame fusions and other rearrangements were predicted to have a breakpoint within intron 17/exon 18 of the FGFR2 gene leaving the FGFR2 kinase domain intact.

Patients received PEMAZYRE in 21-day cycles at a dosage of 13.5 mg orally once daily for 14 consecutive days, followed by 7 days off therapy. PEMAZYRE was administered until disease progression or unacceptable toxicity. The major efficacy outcome measures were overall response rate (ORR) and duration of response (DoR) as determined by an independent review committee (IRC) according to RECIST v1.1.

The median age was 56 years (range: 26 to 77 years), 61% were female, 74% were White, and 95% had a baseline Eastern Cooperative Oncology Group (ECOG) performance status of 0 (42%) or 1 (53%). Ninety-eight percent of patients had intrahepatic cholangiocarcinoma. Eighty-six percent of patients had in-frame FGFR2 gene fusions and the most commonly identified FGFR2 fusion was FGFR2-BICC1 (34%). Fourteen percent of patients had other FGFR2 rearrangements that could not be confidently predicted to be in-frame fusions, including rearrangements without an identifiable partner gene. All patients had received at least 1 prior line of systemic therapy, 27% had 2 prior lines of therapy, and 12% had 3 or more prior lines of therapy. Ninety-six percent of patients had received prior platinum-based therapy including 76% with prior gemcitabine/cisplatin.

Efficacy results are summarized in Table 7.

The median time to response was 2.7 months (range 0.7 – 6.9 months).

Table 7: Efficacy Results in FIGHT-202
Efficacy Parameter | PEMAZYRE N = 107
ORR (95% CI) | 36% (27, 45)
Complete response | 2.8%
Partial response | 33%
Median DoR (months) (95% CI) [The 95% confidence interval (CI) was calculated using the Brookmeyer and Crowley's method. Note: Data are from IRC per RECIST v1.1, and complete and partial responses are confirmed.] | 9.1 (6.0, 14.5)
Patients with DoR ≥ 6 months, n (%) | 24 (63%)
Patients with DoR ≥ 12 months, n (%) | 7 (18%)

14.2 Myeloid/Lymphoid Neoplasms with FGFR1 Rearrangement

FIGHT-203 (NCT03011372), a multicenter open-label, single-arm trial, evaluated the efficacy of PEMAZYRE in 28 patients with MLNs with FGFR1 rearrangement. Inclusion criteria included documented myeloid/lymphoid neoplasms with 8p11 rearrangement shown to be an FGFR1 activating mutation, based on cytogenetic evaluation. Patients could have relapsed after allogeneic hematopoietic stem cell transplantation (allo-HSCT) or after a disease modifying therapy, or were not a candidate for allo-HSCT or other disease modifying therapies.

Patients received PEMAYZRE 13.5 mg once daily in 21-day cycles, either on a continuous schedule (the approved recommended starting dosage) or as an intermittent schedule (14 days on, 7 days off, an unapproved dosage regimen in MLN with FGFR1 rearrangement). PEMAZYRE was administered until disease progression or unacceptable toxicity or until patients were able to receive allo-HSCT. The median age was 65 years (range: 39-78), 64% were female, 68% were White, 3.6% were Black or African American, 11% were Asian, 3.6% were American Indian/Alaska Native, 3.6% were other race, and race was unknown or not collected for 11% of patients; 3.6% were Hispanic, 68% were not Hispanic, 11% were other ethnicity, and ethnicity was not reported in 18%, and 88% had an ECOG performance status of 0 or 1.

In patients with chronic phase in the marrow with or without extramedullary disease (EMD) (N = 18), efficacy was established based on complete response (CR). CR was defined based on the MDS/MPN Working Group response criteria (2015) for MDS/MPN neoplasms with the additional requirement that peripheral eosinophils are < 0.5 × 10^9/L, and, if relevant, CR in EMD using Lugano criteria (Cheson 2014). The CR rate was 78% (14/18; 95% CI: 52, 94). The median time to response of CR was 104 days (range, 44 to 435 days). The median duration of CR was not reached (range, 1+ to 988+ days).

In patients with blast phase in the marrow with or without EMD (N = 4), efficacy was established based on CR. CR was defined as < 5% blasts in the bone marrow, no evidence of disease, and full recovery of peripheral blood counts (platelets > 100,000/microliter and absolute neutrophil counts > 1,000/microliter). Of the 4 patients with blast phase, two patients achieved a CR (duration: 1+ and 94 days).

In patients with EMD only (N = 3), efficacy was established based on CR using Lugano criteria (Cheson 2014). In the 3 patients with EMD only, 1 patient achieved a CR (duration: 64+ days).

For all patients (N = 28 including 3 patients without evidence of morphologic disease), the complete cytogenetic response rate was 79% (22/28; 95% CI: 59, 92).

16 HOW SUPPLIED/STORAGE AND HANDLING

PEMAZYRE tablets are available as follows:

- 4.5 mg: Round, white to off-white debossed on one side with “I” and “4.5” on the other side in bottles of 14 with child-resistant closure, NDC 50881-026-01
- 9 mg: Oval, white to off-white debossed on one side with “I” and “9” on the other side in bottles of 14 with child-resistant closure, NDC 50881-027-01
- 13.5 mg: Round, white to off-white debossed on one side with “I” and “13.5” on the other side in bottles of 14 with child-resistant closure, NDC 50881-028-01

Store PEMAZYRE tablets at room temperature 20°C to 25°C (68°F to 77°F); excursions permitted to 15°C to 30°C (59°F to 86°F).

17 PATIENT COUNSELING INFORMATION

Advise the patient to read the FDA-approved patient labeling (Patient Information).

Ocular Toxicity

Advise patients that PEMAZYRE may cause ocular toxicity including RPED and to immediately inform their healthcare provider if they experience any visual changes. Also advise patients that they should use artificial tear or substitutes, hydrating or lubricating eye gels in order to prevent or treat dry eyes [see Warnings and Precautions (5.1)].

Hyperphosphatemia and Soft Tissue Mineralization

Inform patients that they may experience increase in phosphate levels and of the need to monitor serum phosphate levels. Advise patients to immediately inform their healthcare provider of any symptoms related to acute change in phosphate levels such as muscle cramps, numbness, or tingling around the mouth [see Warnings and Precautions (5.2)].

Nail Disorders

Advise patients that PEMAZYRE may cause nail disorders [see Adverse Reactions (6.1)].

Embryo-Fetal Toxicity

- Advise females to inform their healthcare provider if they are pregnant or become pregnant. Inform female patients of the risk to a fetus and potential loss of pregnancy [see Warnings and Precautions (5.3) and Use in Specific Populations (8.1)].
- Advise females of reproductive potential to use effective contraception during treatment with PEMAZYRE and for 1 week after the last dose [see Use in Specific Populations (8.3)].
- Advise males with female partners of reproductive potential or who are pregnant to use effective contraception during treatment and for 1 week after receiving the last dose of PEMAZYRE [see Use in Specific Populations (8.3)].

Lactation

- Advise patients not to breastfeed during treatment with PEMAZYRE and for 1 week after the last dose [see Use in Specific Populations (8.2)].

Administration

- Instruct patients do not crush, chew, split or dissolve tablets.
- Instruct patients if they miss a dose by 4 or more hours or if they vomit after taking a dose, resume dosing with the next scheduled dose. Extra tablets should not be taken to make up for the missed dose [see Dosage and Administration (2.2)].

Drug Interactions

Advise patients to inform their healthcare providers of all concomitant medications, herbal and dietary supplements. Advise patients to avoid grapefruit products during treatment with PEMAZYRE [see Drug Interactions (7.1)].

Manufactured for:
Incyte Corporation
Wilmington, DE 19803

PEMAZYRE is a registered trademark of Incyte.
U.S. Patent Nos. 9,611,267, 10,131,667, 11,466,004, and 11,628,162
© 2020-2023 Incyte Corporation. All rights reserved.

PATIENT INFORMATION
PEMAZYRE® (pemah zeer)
(pemigatinib) tablets

What is PEMAZYRE?
PEMAZYRE is a prescription medicine that is used to treat adults with:

- bile duct cancer (cholangiocarcinoma) that has spread or cannot be removed by surgery:
  - who have already received a previous treatment, and
  - whose tumor has a certain type of abnormal FGFR2 gene.

- a type of blood cancer called myeloid/lymphoid neoplasms (MLNs):
  - when it has come back or did not respond to treatment, and
  - whose tumor has a certain type of abnormal FGFR1 gene.

Your healthcare provider will test your cancer for certain types of abnormal FGFR1 or FGFR2 genes and make sure that PEMAZYRE is right for you.
It is not known if PEMAZYRE is safe and effective in children.

Before you take PEMAZYRE, tell your healthcare provider about all of your medical conditions, including if you:

- have vision or eye problems
- have kidney problems
- have liver problems
- are pregnant or plan to become pregnant. PEMAZYRE can harm your unborn baby or cause loss of your pregnancy (miscarriage). You should not become pregnant during treatment with PEMAZYRE.
  Females who can become pregnant:
  º Your healthcare provider should do a pregnancy test before you start treatment with PEMAZYRE.
  º You should use an effective method of birth control during treatment and for 1 week after your last dose of PEMAZYRE. Talk to your healthcare provider about birth control methods that may be right for you.
  º Tell your healthcare provider right away if you become pregnant or think that you may be pregnant.
  Males with female partners who can become pregnant:
  º You should use effective birth control when sexually active during treatment with PEMAZYRE and for 1 week after your last dose of PEMAZYRE.

- are breastfeeding or plan to breastfeed. It is not known if PEMAZYRE passes into your breast milk. Do not breastfeed during treatment and for 1 week after your last dose of PEMAZYRE.

Tell your healthcare provider about all the medicines you take, including prescription and over-the-counter medicines, vitamins, and herbal supplements.

How should I take PEMAZYRE?

- Take PEMAZYRE exactly as your healthcare provider tells you.
- For cholangiocarcinoma, PEMAZYRE is taken in cycles of 21 days. Take PEMAZYRE 1 time each day for 14 days, followed by 7 days off treatment, to complete a 21-day treatment cycle.
- For myeloid/lymphoid neoplasms (MLNs), take PEMAZYRE 1 time each day.
- Take PEMAZYRE at about the same time each day.
- Take PEMAZYRE with or without food.
- Swallow tablets whole. Do not crush, chew, split, or dissolve PEMAZYRE tablets.
- You should not eat or drink grapefruit products during treatment with PEMAZYRE.
- Your healthcare provider may change your dose of PEMAZYRE, or may temporarily or completely stop treatment if you get certain side effects.
- If you miss a dose of PEMAZYRE, you can take the missed dose within 4 hours on the same day. If more than 4 hours have passed, do not make up the dose. Take your regular dose of PEMAZYRE the next day at the usual time. Do not take more PEMAZYRE than prescribed to make up for the missed dose.
- If you vomit after taking PEMAZYRE, do not take another PEMAZYRE tablet. Take your regular dose of PEMAZYRE the next day at the usual time.

What are the possible side effects of PEMAZYRE?

PEMAZYRE may cause serious side effects, including:

- Eye problems. Certain eye problems are common with PEMAZYRE but can also be serious. Eye problems include dry eye or inflamed eyes, inflamed cornea (front part of the eye), increased tears, and a disorder of the retina (an internal part of the eye). You will need to see an eye specialist for a complete eye exam before you begin treatment with PEMAZYRE, every 2 months for the first 6 months, and then every 3 months during treatment with PEMAZYRE.
  - You should use artificial tears or substitutes, hydrating or lubricating eye gels as needed, to help prevent or treat dry eyes.
  - Tell your healthcare provider right away if you develop any changes in your vision during treatment with PEMAZYRE, including: blurred vision, flashes of light, or see black spots. You may need to see an eye specialist right away.

- High phosphate levels in your blood (hyperphosphatemia) and buildup of minerals in different tissues in your body. Hyperphosphatemia is common with PEMAZYRE but can also be serious. High levels of phosphate in your blood may lead to buildup of minerals such as calcium, in different tissues in your body. Your healthcare provider will check your blood phosphate levels during treatment with PEMAZYRE.
  - Your healthcare provider may prescribe changes in your diet or phosphate lowering therapy, or change, interrupt or stop PEMAZYRE if needed.
  - Tell your healthcare provider right away if you develop any muscle cramps, or numbness or tingling around your mouth.

The most common side effects of PEMAZYRE for cholangiocarcinoma include:

- hair loss
- diarrhea
- nails separate from the bed or poor formation of the nail
- feeling tired
- change in sense of taste
- nausea
- constipation
- mouth sores

- dry eyes
- dry mouth
- decrease in appetite
- vomiting
- joint pain
- stomach-area (abdominal) pain
- low phosphate in blood
- back pain
- dry skin

The most common side effects of PEMAZYRE for myeloid/lymphoid neoplasms (MLNs) include:

- nails separate from the bed or poor formation of the nail
- hair loss
- mouth sores
- diarrhea
- dry eyes
- tiredness
- anemia
- stomach-area (abdominal) pain
- rash
- constipation
- dry mouth

- nose bleeds
- disorder of the retina
- pain in feet or hands
- decreased appetite
- dry skin
- indigestion
- back pain
- nausea
- blurry vision
- swelling in feet, legs, hands, or arms
- dizziness

These are not all the possible side effects of PEMAZYRE. For more information, ask your healthcare provider or pharmacist.

Call your doctor for medical advice about side effects. You may report side effects to FDA at 1‑800-FDA-1088.

How should I store PEMAZYRE?

- Store PEMAZYRE at room temperature between 68°F to 77°F (20°C to 25°C).

Keep PEMAZYRE and all medicines out of the reach of children.

General information about the safe and effective use of PEMAZYRE
Medicines are sometimes prescribed for purposes other than those listed in a Patient Information leaflet. Do not use PEMAZYRE for a condition for which it is not prescribed. Do not give PEMAZYRE to other people, even if they have the same symptoms you have. It may harm them. If you would like more information, talk with your healthcare provider. You can ask your pharmacist or healthcare provider for information that is written for healthcare professionals.

What are the ingredients in PEMAZYRE?

Active ingredient: pemigatinib

Inactive ingredients: magnesium stearate, microcrystalline cellulose, and sodium starch glycolate.

Manufactured for: Incyte Corporation, Wilmington, DE 19803

PEMAZYRE is a registered trademark of Incyte.

© 2020-2022 Incyte Corporation. All rights reserved.

For more information, call Incyte at 1-855-463-3463 or go to www.PEMAZYRE.com

This Patient Information has been approved by the U.S. Food and Drug Administration. Revised: 08/2022

4.5 mg Tablet Bottle Label

Rx only

NDC 50881-026-01

Pemazyre® (pemigatinib) tablets

4.5 mg

14 tablets

9 mg Tablet Bottle Label

Rx only

NDC 50881-027-01

Pemazyre® (pemigatinib) tablets

9 mg

14 tablets

13.5 mg Tablet Bottle Label

Rx only

NDC 50881-028-01

Pemazyre® (pemigatinib) tablets

13.5 mg

14 tablets